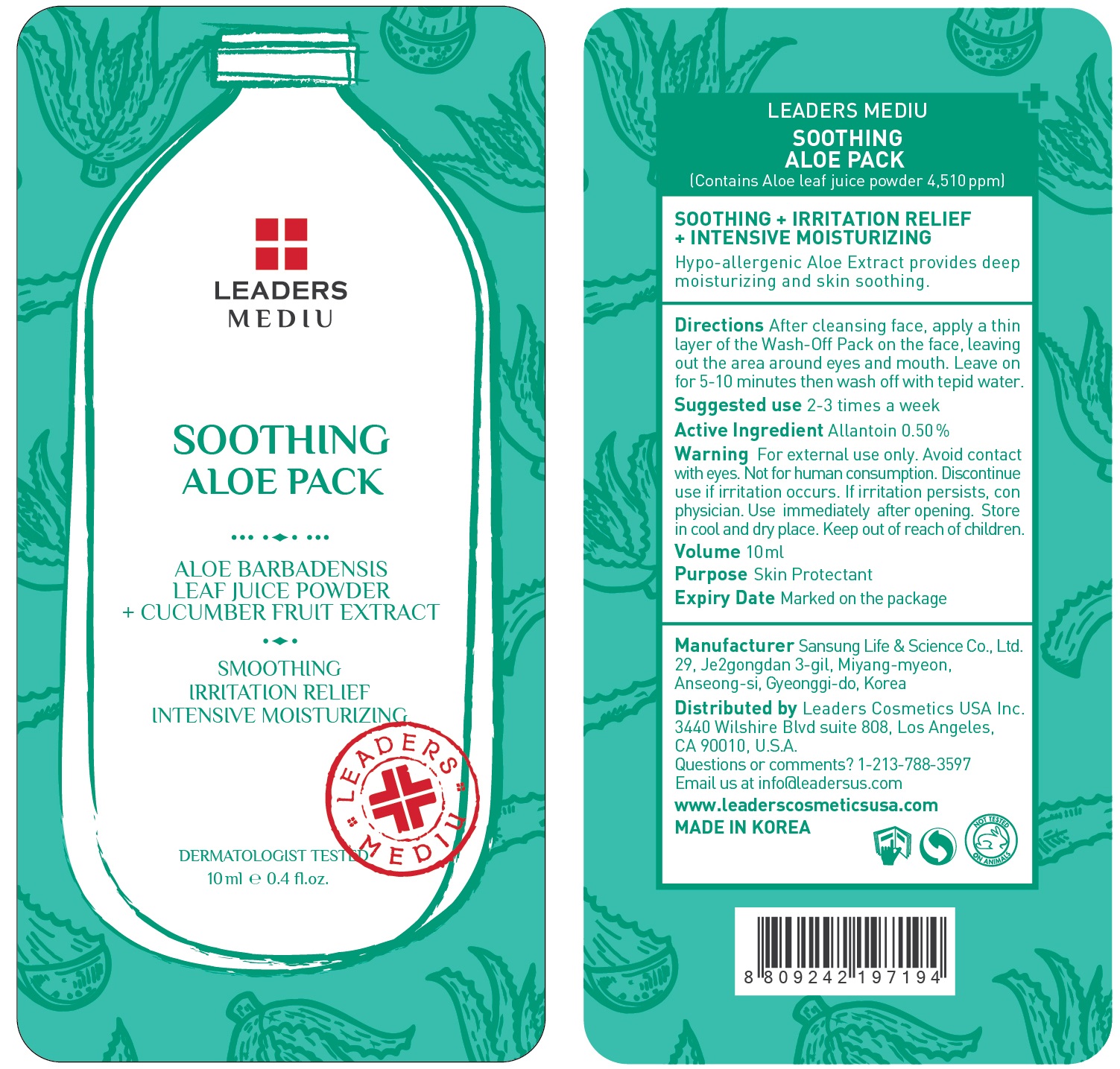 DRUG LABEL: Leaders Mediu Soothing Aloe Pack
NDC: 69424-530 | Form: GEL
Manufacturer: SANSUNG LIFE & SCIENCE CO., LTD.
Category: otc | Type: HUMAN OTC DRUG LABEL
Date: 20160201

ACTIVE INGREDIENTS: Allantoin 50 mg/10 mL
INACTIVE INGREDIENTS: Water; Glycerin

ACTIVE INGREDIENT

Active Ingredient: Allantoin 0.50%

INACTIVE INGREDIENT

Inactive Ingredients: Water, Glycerin, 1,2-Hexanediol, Butylene Glycol, Arginine, Carbomer, PEG-60 Hydrogenated Castor Oil , Aloe barbadensis Leaf Juice Powder, Sodium Polyacrylate, Portulaca Oleracea extract , Cucumis Sativus (Cucumber) Fruit extract, Fragrance, Buteth-3, Glyceryl Acrylate/Acrylic Acid Copolymer, Maltodextrin, PVM/MA Copolymer, Disodium EDTA, Sodium Benzotriazolyl Butylphenol Sulfonate, Tributyl Citrate, CI 19140, CI 42090, Sodium Hyaluronate

PURPOSE

Purpose: Skin Protectant

WARNINGS

Warnings: For external use only. Avoid contact with eyes. Not for human consumption. Discontinue use if irritation occurs. If irritation persists, consult a physician.

Use immediately after opening. Store in cool and dry place. Keep out of reach of children.

KEEP OUT OF REACH OF CHILDREN

Directions

Directions: After cleansing face, apply a thin layer of the Wash-Off Pack on the face, leaving out the area around eyes and mouth. Leave on for 5-10 minutes then wash off with tepid water. *Suggested use is 2-3 times a week

Directions

Directions: After cleansing face, apply a thin layer of the Wash-Off Pack on the face, leaving out the area around eyes and mouth. Leave on for 5-10 minutes then wash off with tepid water. *Suggested use is 2-3 times a week